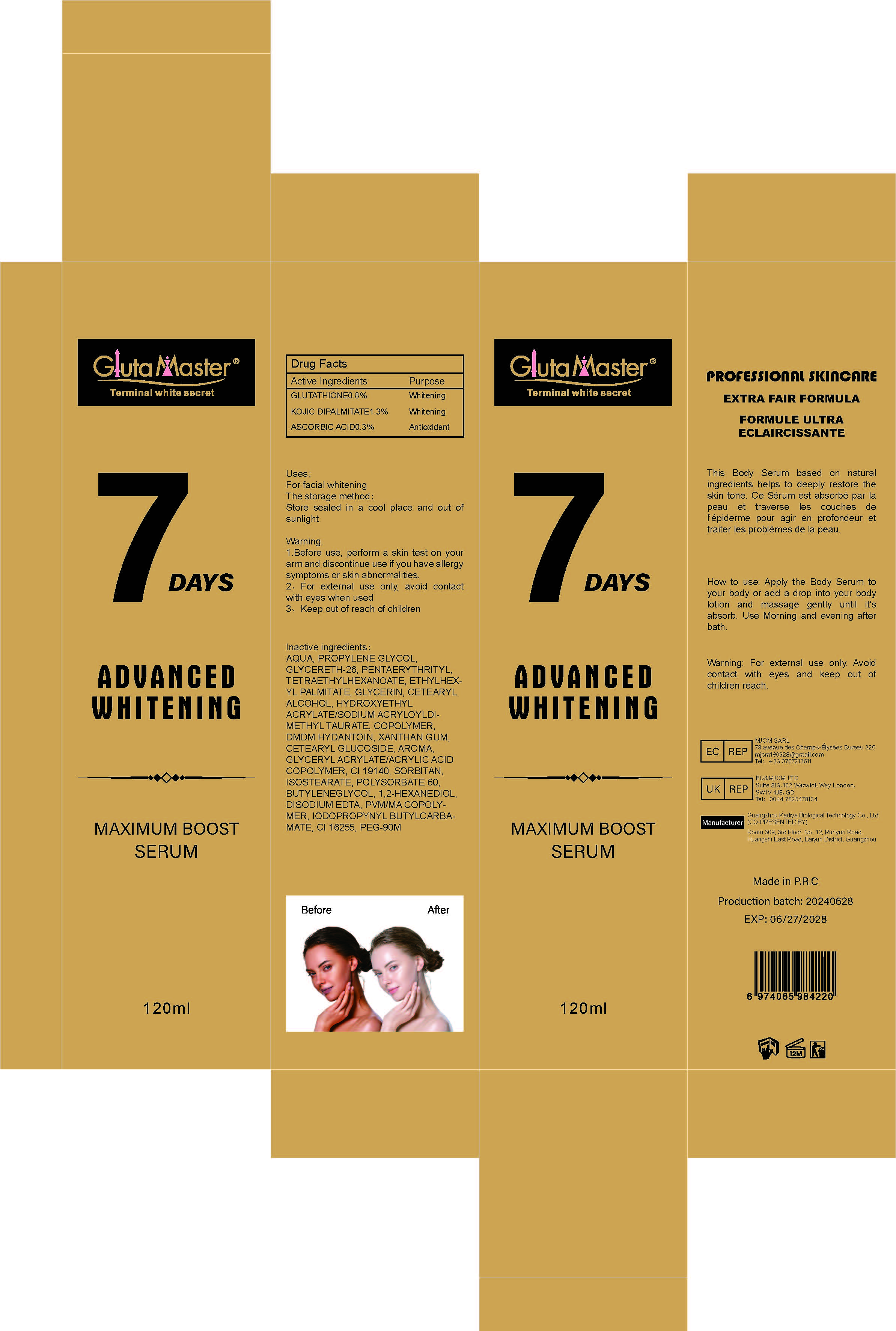 DRUG LABEL: 7 DAYS ADUANCED WHITENING MAXIMUM BOOST SERUM
NDC: 84423-021 | Form: LIQUID
Manufacturer: Guangzhou Kadiya Biotechnology Co., Ltd.
Category: otc | Type: HUMAN OTC DRUG LABEL
Date: 20240710

ACTIVE INGREDIENTS: GLUTATHIONE 0.96 mg/120 mg; ASCORBIC ACID 3.6 mg/120 mg; KOJIC DIPALMITATE 1.56 mg/120 mg
INACTIVE INGREDIENTS: POLYSORBATE 60; ETHYLHEXYL PALMITATE; XANTHAN GUM; HYDROXYETHYL ACRYLATE/SODIUM ACRYLOYLDIMETHYL TAURATE COPOLYMER (45000 MPA.S AT 1%); CETEARYL GLUCOSIDE; 1,2-HEXANEDIOL; WATER; PENTAERYTHRITYL TETRAETHYLHEXANOATE; GLYCERYL ACRYLATE/ACRYLIC ACID COPOLYMER (300000 CP AT 2%); PROPYLENE GLYCOL; GLYCERIN; CETOSTEARYL ALCOHOL; DMDM HYDANTOIN; IODOPROPYNYL BUTYLCARBAMATE; SORBITAN ISOSTEARATE; POLYETHYLENE GLYCOL 4000000; 1,3-BUTYLENEGLYCOL DIMETHACRYLATE; EDETATE DISODIUM; GLYCERETH-26; FD&C YELLOW NO. 5; METHYL VINYL ETHER AND MALEIC ANHYDRIDE COPOLYMER (1100000 WAMW); PONCEAU 4R

Uses：
For facial whitening
Indications: For facial whitening

INACTIVE INGREDIENT

AQUA、PROPYLENE GLYCOL、GLYCERETH-26、PENTAERYTHRITYL、TETRAETHYLHEXANOATE、ETHYLHEXYL PALMITATE、GLYCERIN、CETEARYL ALCOHOL、HYDROXYETHYL ACRYLATE/SODIUM ACRYLOYLDIMETHYL TAURATE、COPOLYMER、DMDM HYDANTOIN、XANTHAN GUM、CETEARYL GLUCOSIDE、AROMA、GLYCERYL ACRYLATE/ACRYLIC ACID COPOLYMER、CI 19140、SORBITAN、ISOSTEARATE、POLYSORBATE 60、BUTYLENEGLYCOL、1,2-HEXANEDIOL、DISODIUM EDTA、PVM/MA COPOLYMER、IODOPROPYNYL BUTYLCARBAMATE、CI 16255、PEG-90M

Warning.
1.Before use, perform a skin test on your arm and discontinue use if you have allergy symptoms or skin abnormalities.
2、For external use only, avoid contact with eyes when used
3、Keep out of reach of children

INDICATIONS AND USAGE

Apply the Body Serum to
your body or add a drop into your body
lotion and massage gently until it’s
absorb. Use Morning and evening after
bath.

KEEP OUT OF REACH OF CHILDREN SECTION

Drug Facts
Active Ingredients
GLUTATHIONE 0.8%
KOJIC DIPALMITATE 1.3%
ASCORBIC ACID 0.3%

DOSAGE AND ADMINISTRATION

Use Morning and evening after
bath.

Drug Facts
Active Ingredients
GLUTATHIONE 0.8%
KOJIC DIPALMITATE 1.3%
ASCORBIC ACID 0.3%

Uses：
For facial whitening
Indications: For facial whitening
The storage method：
Store sealed in a cool place and out of sunlight

Warning.
1.Before use, perform a skin test on your arm and discontinue use if you have allergy symptoms or skin abnormalities.
2、For external use only, avoid contact with eyes when used
3、Keep out of reach of children

Inactive ingredients：
AQUA、PROPYLENE GLYCOL、GLYCERETH-26、PENTAERYTHRITYL、TETRAETHYLHEXANOATE、ETHYLHEXYL PALMITATE、GLYCERIN、CETEARYL ALCOHOL、HYDROXYETHYL ACRYLATE/SODIUM ACRYLOYLDIMETHYL TAURATE、COPOLYMER、DMDM HYDANTOIN、XANTHAN GUM、CETEARYL GLUCOSIDE、AROMA、GLYCERYL ACRYLATE/ACRYLIC ACID COPOLYMER、CI 19140、SORBITAN、ISOSTEARATE、POLYSORBATE 60、BUTYLENEGLYCOL、1,2-HEXANEDIOL、DISODIUM EDTA、PVM/MA COPOLYMER、IODOPROPYNYL BUTYLCARBAMATE、CI 16255、PEG-90M